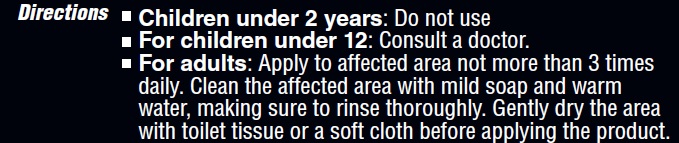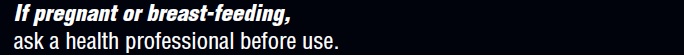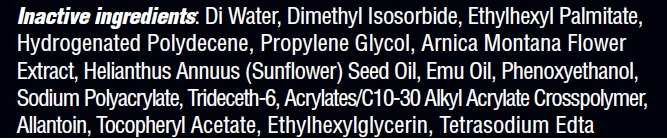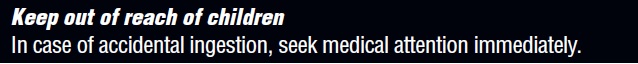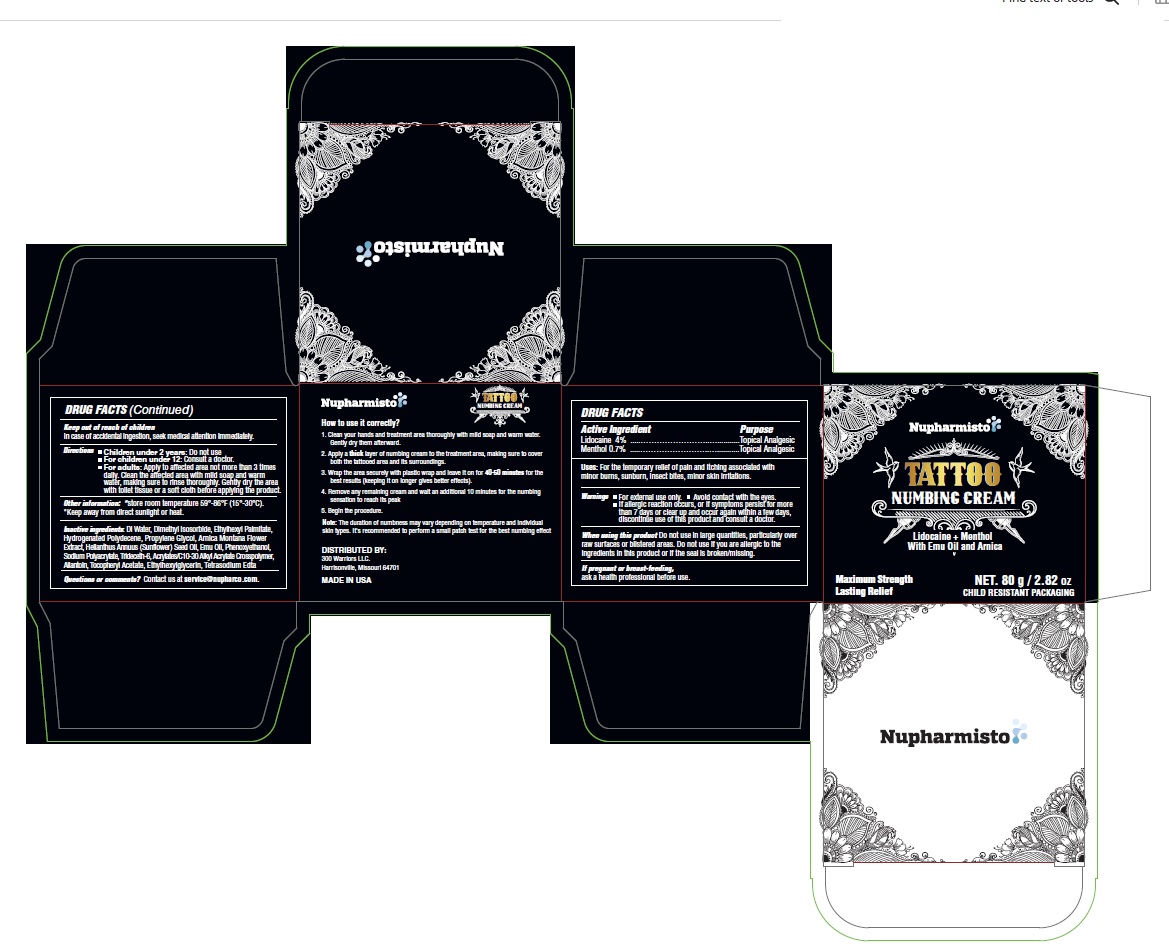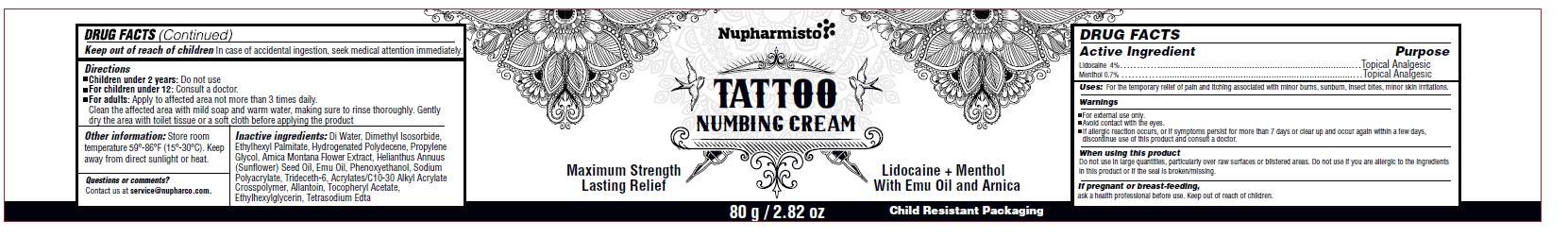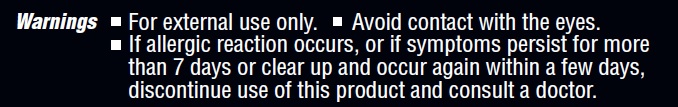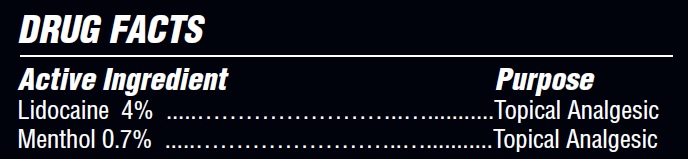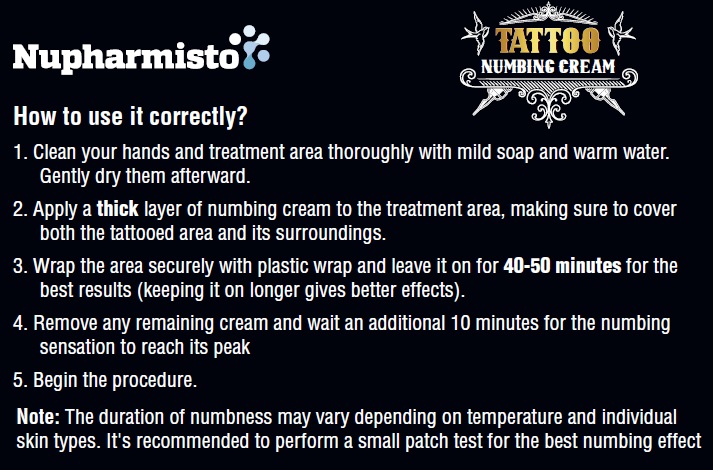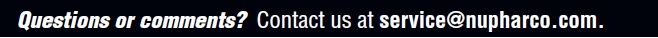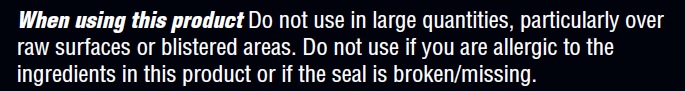 DRUG LABEL: Nupharmisto Tattoo Numbing Cream 80g
NDC: 71331-116 | Form: CREAM
Manufacturer: Orange Lab, Inc
Category: otc | Type: HUMAN OTC DRUG LABEL
Date: 20240501

ACTIVE INGREDIENTS: MENTHOL 0.7 g/100 g; LIDOCAINE 4 g/100 g
INACTIVE INGREDIENTS: ACRYLATES/C10-30 ALKYL ACRYLATE CROSSPOLYMER (60000 MPA.S); ETHYLHEXYL PALMITATE; HYDROGENATED POLYDECENE (1500 CST); SODIUM POLYACRYLATE (8000 MW); ALLANTOIN; TRIDECETH-6; EMU OIL; PHENOXYETHANOL; EDETATE SODIUM TETRAHYDRATE; DIMETHYL ISOSORBIDE; PROPYLENE GLYCOL; SUNFLOWER OIL; .ALPHA.-TOCOPHEROL ACETATE; ETHYLHEXYLGLYCERIN; WATER; ARNICA MONTANA FLOWER

Nupharmisto Lidocaine Tattoo Numbing Cream 4% 80g